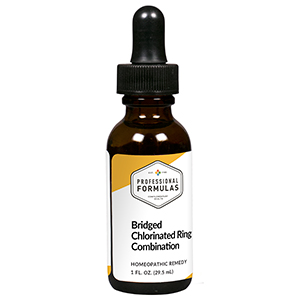 DRUG LABEL: Bridged Chlorinated Ring Combination
NDC: 63083-9313 | Form: LIQUID
Manufacturer: Professional Complementary Health Formulas
Category: homeopathic | Type: HUMAN OTC DRUG LABEL
Date: 20190815

ACTIVE INGREDIENTS: BLACK COHOSH 3 [hp_X]/29.5 mL; GELSEMIUM SEMPERVIRENS ROOT 3 [hp_X]/29.5 mL; BERBERIS VULGARIS ROOT BARK 10 [hp_X]/29.5 mL; CHELIDONIUM MAJUS WHOLE 10 [hp_X]/29.5 mL; PARAQUAT DICHLORIDE 12 [hp_X]/29.5 mL; THUJA OCCIDENTALIS LEAF 12 [hp_X]/29.5 mL; DICHLORVOS 16 [hp_X]/29.5 mL
INACTIVE INGREDIENTS: ALCOHOL; WATER

R313

ACTIVE INGREDIENTS

Cimicifuga racemosa 3X
Gelsemium sempervirens 3X
Berberis vulgaris 10X
Chelidonium majus 10X
Paraquat 12X
Thuja occidentalis 12X
Dichlorvos methoxychlor 16X

QUESTIONS

Professional Formulas

PO Box 2034 Lake Oswego, OR 97035

INDICATIONS

For the temporary relief of upper respiratory irritation, minor sore throat, stomach discomfort, vomiting, diarrhea, or weakness.*

PURPOSE

*Claims based on traditional homeopathic practice, not accepted medical evidence. Not FDA evaluated.

WARNINGS

Consult a doctor if condition worsens or if symptoms persist. Keep out of the reach of children. In case of overdose, get medical help or contact a poison control center right away. If pregnant or breastfeeding, ask a healthcare professional before use.

Keep out of the reach of children.

PREGNANCY OR BREAST FEEDING

If pregnant or breastfeeding, ask a healthcare professional before use.

DIRECTIONS

Place drops under tongue 30 minutes before/after meals. Adults and children 12 years and over: Take 10 drops up to 3 times per day. Consult a physician for use in children under 12 years of age.

OTHER INFORMATION

Tamper resistant. If seal is broken, do not use. After opening, close container tightly and store at room temperature away from heat.

INACTIVE INGREDIENTS

40% ethanol, purified water.

LABEL

Est 1985

Professional Formulas

Complementary Health

Bridged Chlorinated Ring Combination

Homeopathic Remedy

1 FL. OZ. (29.5 mL)